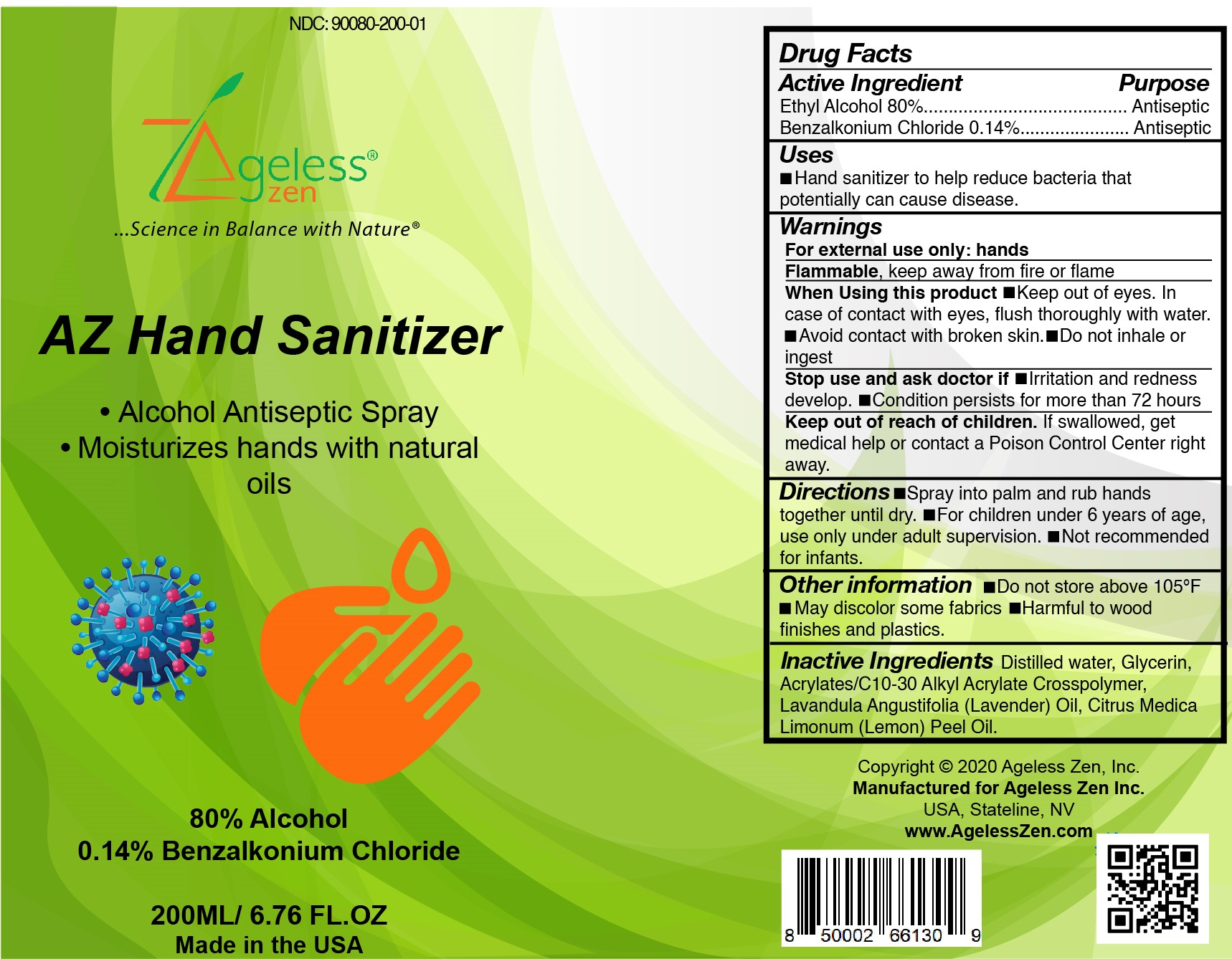 DRUG LABEL: AZ Hand Sanitizer
NDC: 90080-200 | Form: SPRAY
Manufacturer: Ageless Zen Inc.
Category: otc | Type: HUMAN OTC DRUG LABEL
Date: 20201110

ACTIVE INGREDIENTS: ALCOHOL 80 mL/200 mL; BENZALKONIUM CHLORIDE 0.14 1/200 mL
INACTIVE INGREDIENTS: WATER; GLYCERIN; CARBOMER INTERPOLYMER TYPE A (ALLYL SUCROSE CROSSLINKED); LAVENDER OIL; LEMON OIL

Ageless Zen
AZ Hand Sanitizer

Active Ingredient

Ethyl alcohol 80% v/v. Purpose: Antiseptic

Benzalkonium Chloride 0.14% v/v. Purpose: Antiseptic

Purpose

Alcohol Antiseptic Spray

Uses

Hand Sanitizer to help reduce bacteria that potentially can cause disease

Warnings

For external use only: hands.

Flammable, keep away from fire or flame.

When using this product

Keep out of eyes. In case of contact with eyes, flush thoroughly with water. Avoid contact with broken skin. Do not inhale or ingest

Stop use and ask a doctor if

Irritation and redness develop Condition persists for more than 72 hours.

Keep out of reach of children.

If swallowed, get medical help or contact a Poison Control Center right away.

Directions

Spray into palm and rub hands together until dry. For children under 6 years of age, use only under adult supervision. Not recommended for infants

Other information

Do not store above 105F. May discolor some fabrics. Harmful to wood finishes and plastics.

Inactive Ingredients

Distilled Water, Glycerin, Acrylates/C10-30 Alkyl Acrylate Crosspolymer, Lavandula Angustifolia (Lavender) Oil, Citrus Medica Limonum (Lemon) Peel Oil

Ageless Zen AZ Hand Sanitizer

Alcohol Antiseptic Spray

Moisturizes hands with natural oils

80% Alchol

0.14% Benzalkonium Chloride

200ML/ 6.76 FL.OZ

Made in the USA